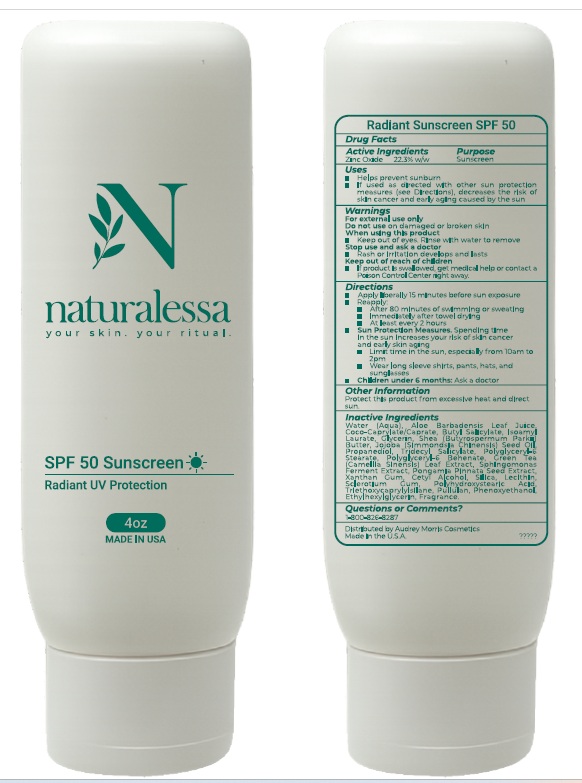 DRUG LABEL: Naturalessa SPF50 Moisturizer
NDC: 83695-003 | Form: CREAM
Manufacturer: Audrey Morris Cosmetics International, LLC
Category: otc | Type: HUMAN OTC DRUG LABEL
Date: 20260226

ACTIVE INGREDIENTS: ZINC OXIDE 22.3 g/100 g
INACTIVE INGREDIENTS: WATER; ALOE VERA LEAF; COCOYL CAPRYLOCAPRATE; BUTYL SALICYLATE; ISOAMYL LAURATE; GLYCERIN; SHEA BUTTER; JOJOBA OIL; PROPANEDIOL; TRIDECYL SALICYLATE; POLYGLYCERYL-6 STEARATE; POLYGLYCERYL-6 BEHENATE; BEHENIC ACID; GREEN TEA LEAF; PONGAMIA PINNATA SEED; XANTHAN GUM; CETYL ALCOHOL; SILICON DIOXIDE; SOYBEAN LECITHIN; BETASIZOFIRAN; POLYHYDROXYSTEARIC ACID (2300 MW); TRIETHOXYCAPRYLYLSILANE; PULLULAN; PHENOXYETHANOL; ETHYLHEXYLGLYCERIN; FERMENT COMPLEX 6/PF

Active Ingredients Purpose

Zinc Oxide 22.3% W/W Sunscreen

Uses

- Helps prevent sunburn
- If used as directed with other sun protection measures (See Directions), decreases the risk of skin cancer and early aging caused by the sun.

Warnings

For Extranal use only
Do not use on damaged or broken skin.
When using this product

- Keep out of eyes. Rinse with water to remove

Stop use and ask doctor

- Rash or irritation develops and lasts

Keep out of reach if children

- If product gets swallowed, get medical help or contact a Poison Control Center right away

Directions

- Apply liberally 15 minutes before sun exposure
- Reapply:
- After 80 minutes of swimming or sweating
- Immediately after towel drying.
- At least every 2 hours
- Sun Protection Measures: Spending time in the sun increases your risk of skin cancer and early skin aging. To decrease this risk, regularly use a sunscreen with broad spectrum SPF of 15 or higher and other sun protection measures including:
- Limit time in the sun, especially from 10:00a.m – 2:00p.m
- Wear long sleave shirts, pants, hats, and sunglasses.
- Children under 6 Months: Ask a doctor

Other information

Protect this product from excessive heat and direact sun

Inactive Ingredients

Water (Aqua), Aloe Barbadensis Leaf Juice, Coco-Caprylate/Caprate, Butyl Salicylate, Isoamyl Laurate, Glycerin, Shea (Butyrospermum Parkii) Butter, Jojoba (Simmondsia Chinensis) Seed Oil, Propanediol, Tridecyl Salicylate, Polyglyceryl-6 Stearate, Polyglyceryl-6 Behenate, Green Tea (Camellia Sinensis) Leaf Extract, Sphingomonas Ferment Extract, Pongamia Pinnata Seed Extract, Xanthan Gum, Cetyl Alcohol, Silica, Lecithin, Sclerotium Gum, Polyhydroxystearic Acid, Triethoxycaprylylsilane, Pullulan, Phenoxyethanol, Ethylhexylglycerin, Fragrance.

Questions or Comments?

1-800-826-8287